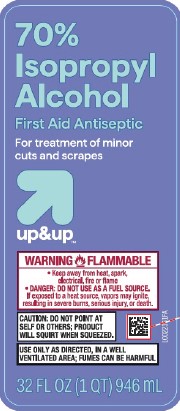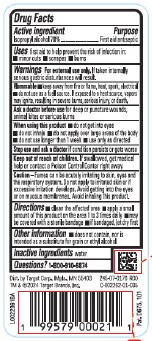 DRUG LABEL: 70%
NDC: 11673-810 | Form: LIQUID
Manufacturer: Target Corporation
Category: otc | Type: HUMAN OTC DRUG LABEL
Date: 20260218

ACTIVE INGREDIENTS: ISOPROPYL ALCOHOL 70 mL/100 mL
INACTIVE INGREDIENTS: WATER

UP & UP 810.003/810AA
70% Isopropyl Alcohol

Active ingredient

Isopropyl alcohol 70%

purpose

First Aid Antiseptic

Uses

first aid to help prevent the risk of infection in:

- minor cuts
- scrapes
- burns

Warnings

For external use only. If taken internally serious gastric disturbances will result.

Flammable

- keep away from fire or flame, heat, spark, electrical
- do not use as a fuel source. If exposed to a heat source, vapors may ignite, resulting in severe burns, serious injury, or death.

Ask a Doctor before use

for deep or puncture wounds, animal bites or serious burns

When using this product

- do not get into eyes
- do not inhale
- do not apply over large areas of the body
- do not use longer than 1 week
- use only as directed

Stop use and ask a doctor

If condition persists or gets worse

Keep out of reach of children.

If swallowed, get medical help or contact a Poison Control Center right away.

Caution

Fumes can be acutely irritating to skin, eyes and the respiratory system. Do not apply to irritated skin or if excessive irritation develops. Avoid getting into the eyes or on mucous membranes. Avoid inhaling this product.

Directions

- clean the affected area
- spray a small amount of this product on the affected area 1 to 3 times daily
- may be covered with a sterile bandage
- if bandaged, let dry first

Other information

- does not contain, nor is intended as a substitute for grain or ethyl alcohol

Inactive ingredient

water

Questions?

1-800-910-6874

ADVERSE REACTION

Dist. by Target Corp., Mpls., MN 55403

TM & ©2024 Target Brands, Inc.

Pat. D675, 101

principal display panel

70% Isopropyl Alcohol

First Aid Antiseptic

For treatment of minor cuts and scrapes

up & up™

WARNING FLAMMABLE

- Keep away from heat, spark, electrical, fire or flame
- DANGER: DO NOT USE AS A FUEL SOURCE

If exposed to a heat source, vapors may ignite, resulting in severe burns, serious injury, or death.

CAUTION: Do not point at self or others; product will squirt when squeezed.

Use only as directed, in a well-ventilated area; fumes may be harmful.

32 FL OZ (1 QT) 946 mL